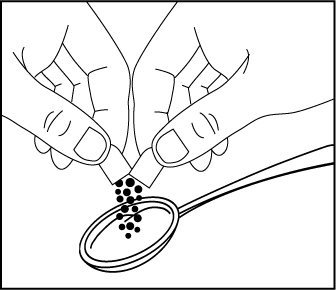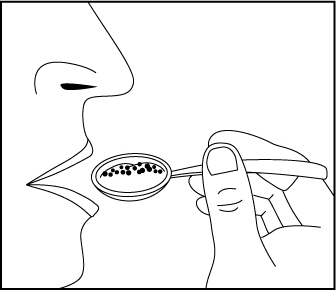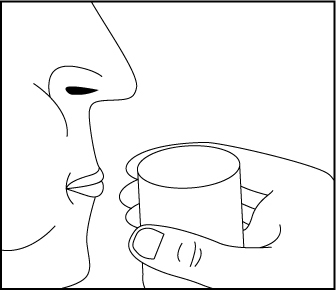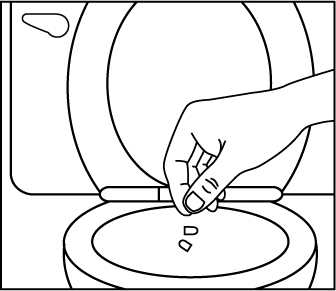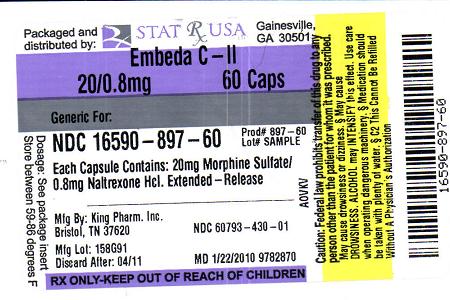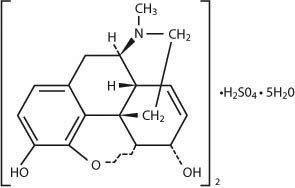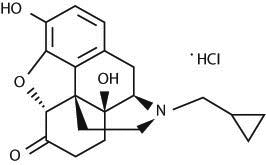 DRUG LABEL: EMBEDA
NDC: 16590-897 | Form: CAPSULE, EXTENDED RELEASE
Manufacturer: STAT RX USA LLC
Category: prescription | Type: HUMAN PRESCRIPTION DRUG LABEL
Date: 20100122
DEA Schedule: CII

ACTIVE INGREDIENTS: MORPHINE SULFATE 20 mg/1 1; NALTREXONE HYDROCHLORIDE .8 mg/1 1

11 DESCRIPTION

EMBEDA Capsules contain pellets of morphine sulfate and naltrexone hydrochloride at a ratio of 100:4. Morphine sulfate is an agonist and naltrexone hydrochloride is an antagonist at the mu-opioid receptor.

The chemical name of morphine sulfate is 7,8-didehydro-4,5 α-epoxy-17-methyl-morphinan-3,6 α-diol sulfate (2:1) (salt) pentahydrate. The empirical formula is (C17H19NO3)2●H2SO4●5H2O and its molecular weight is 758.85.

Morphine sulfate is an odorless, white, crystalline powder with a bitter taste. It has a solubility of 1 in 21 parts of water and 1 in 1000 parts of alcohol, but is practically insoluble in chloroform or ether. The octanol: water partition coefficient of morphine is 1.42 at physiologic pH and the pKb is 7.9 for the tertiary nitrogen (mostly ionized at pH 7.4). Its structural formula is:

STRUCTURE IMAGE 1

The chemical name of naltrexone hydrochloride is (5α)-17-(Cyclopropylmethyl)-4,5-epoxy-3,14-dihydroxymorphinan-6-one hydrochloride. The empirical formula is C20H23NO4•HCl and its molecular weight is 377.46.

Naltrexone hydrochloride is a white to slightly off-white powder that is soluble in water. Its structural formula is

STRUCTURE IMAGE 2

Each capsule contains the following inactive ingredients common to all strengths: talc, ammonio methacrylate copolymer, sugar spheres, ethylcellulose, sodium chloride, polyethylene glycol, hydroxypropyl cellulose, dibutyl sebacate, methacrylic acid copolymer, diethyl phthalate, magnesium stearate, sodium lauryl sulfate, and ascorbic acid. The capsule shells contain gelatin, titanium dioxide, and grey ink, D and C yellow #10 (EMBEDA 20 mg/0.8 mg), FD and C red #3, FD and C blue #1 (EMBEDA 30 mg/1.2 mg), D and C red #28, FD and C red #40, FD and C blue #1 (EMBEDA 50 mg/2 mg), D and C red #28, FD and C red #40, FD and C blue #1 (EMBEDA 60 mg/2.4 mg), FD and C blue #1, FD and C red #40, FD and C yellow #6 (EMBEDA 80 mg/3.2 mg), D and C yellow #10, FD and C blue #1 (EMBEDA 100 mg/4 mg).

EMBEDA contains no gluten.

12 CLINICAL PHARMACOLOGY 12.1 Mechanism Of Action

Morphine sulfate, a pure opioid agonist, is relatively selective for the mu receptor, although it can interact with other opioid receptors at higher doses. In addition to analgesia, the widely diverse effects of morphine sulfate include analgesia, dysphoria, euphoria, somnolence, respiratory depression, diminished gastrointestinal motility, altered circulatory dynamics, histamine release, physical dependence, and alterations of the endocrine and autonomic nervous systems.

Morphine produces both its therapeutic and its adverse effects by interaction with one or more classes of specific opioid receptors located throughout the body. Morphine acts as a pure agonist, binding with and activating opioid receptors at sites in the peri-aqueductal and peri-ventricular grey matter, the ventro-medial medulla and the spinal cord to produce analgesia.

Effects on the Central Nervous System

The principal actions of therapeutic value of morphine are analgesia and sedation (i.e., sleepiness and anxiolysis). Specific CNS opiate receptors and endogenous compounds with morphine-like activity have been identified throughout the brain and spinal cord and are likely to play a role in the expression of analgesic effects. In addition, when morphine binds to mu-opioid receptors, it results in positive subjective effects, such as drug liking, euphoria, and high. Morphine produces respiratory depression by direct action on brainstem respiratory centers. The mechanism of respiratory depression involves a reduction in the responsiveness of the brainstem respiratory centers to increases in carbon dioxide tension, and to electrical stimulation. Morphine depresses the cough reflex by direct effect on the cough center in the medulla. Antitussive effects may occur with doses lower than those usually required for analgesia. Morphine causes miosis, even in total darkness, and little tolerance develops to this effect. Pinpoint pupils are a sign of opioid overdose but are not pathognomonic (e.g., pontine lesions of hemorrhagic or ischemic origins may produce similar findings). Marked mydriasis rather than miosis may be seen with worsening hypoxia in the setting of EMBEDA overdose [see OVERDOSAGE (10)].

Effects on the Gastrointestinal Tract and Other Smooth Muscle

Gastric, biliary, and pancreatic secretions are decreased by morphine. Morphine causes a reduction in motility associated with an increase in tone in the antrum of the stomach and duodenum. Digestion of food in the small intestine is delayed and propulsive contractions are decreased. Propulsive peristaltic waves in the colon are decreased, while tone is increased to the point of spasm. The end result is constipation. Morphine can cause a marked increase in biliary tract pressure as a result of spasm of the sphincter of Oddi.

Effects on the Cardiovascular System

Morphine produces peripheral vasodilation which may result in orthostatic hypotension or syncope. Release of histamine may be induced by morphine and can contribute to opioid-induced hypotension. Manifestations of histamine release and/or peripheral vasodilation may include pruritus, flushing, red eyes and sweating.

Mechanism of Action of Naltrexone

Naltrexone is a pure, centrally acting mu-opioid antagonist that reverses the subjective and analgesic effects of mu-opioid receptor agonists by competitively binding at mu-opioid receptors.

12.2 Pharmacodynamics

Plasma Level-Analgesia Relationships

In any particular patient, both analgesic effects and plasma morphine concentrations are related to the morphine dose.

While plasma morphine-efficacy relationships can be demonstrated in non-tolerant individuals, they are influenced by a wide variety of factors and are not generally useful as a guide to the clinical use of morphine. The effective dose in opioid-tolerant patients may be 10-50 times as great (or greater) than the appropriate dose for opioid-naïve individuals. Dosages of morphine should be chosen and must be titrated on the basis of clinical evaluation of the patient and the balance between therapeutic and adverse effects.

For any fixed dose and dosing interval, EMBEDA will have, at steady-state, a lower Cmax and a higher Cmin than conventional immediate-release morphine.

The pharmacodynamic effect of naltrexone in the setting of crushed EMBEDA was examined in two clinical trials. In a randomized double-blind, triple-dummy, four-way cross-over study, 32 non-dependent recreational opioid users received 120 mg of EMBEDA whole and crushed, 120 mg of immediate-release morphine sulfate and placebo. Overall, 87.5% of subjects had some degree of reduced drug liking after receiving crushed EMBEDA, while 12.5% had no reduction in drug liking. There was considerable individual variability in the degree of reduction in drug liking, ranging between 10 and 50%. Similarly, 69% of subjects showed some degree of a decrease in euphoria with crushed EMBEDA compared to IR morphine and 31% of subjects did not report a reduction in euphoria. There was similar individual variability in the degree of reduction in euphoria.

A randomized double-blind, placebo-controlled, three-way cross-over trial in 28 non-dependent recreational opioid-users was performed using 30 mg of IV morphine alone and 30 mg of IV morphine in combination with 1.2 mg of IV naltrexone to simulate parenteral use of crushed EMBEDA. The combination of morphine with naltrexone resulted in 71% of subjects reporting a reduction in euphoria compared to morphine alone. Note that the intravenous injection of crushed EMBEDA may result in serious injury and death due to a morphine overdose or an embolic event. Intravenous injection of crushed EMBEDA may preciptitate a severe withdrawal syndrome in opioid-dependent patients.

The clinical significance of the degree of reduction in drug liking and euphoria reported in these studies has not yet been established. There is no evidence that the naltrexone in EMBEDA reduces the abuse liability of EMBEDA.

12.3 Pharmacokinetics

Absorption

EMBEDA Capsules contain extended-release pellets of morphine sulfate that release morphine slowly compared to an oral morphine solution. Following the administration of oral morphine solution, approximately 50% of the morphine absorbed reaches the systemic circulation within 30 minutes. However, following the administration of an equal amount of EMBEDA to healthy volunteers, this occurs, on average, after 8 hours. As with most forms of oral morphine, because of pre-systemic elimination, only about 20 to 40% of the administered dose reaches the systemic circulation.

EMBEDA is bioequivalent to a similar morphine sulfate extended release capsules product with regard to rate and extent of plasma morphine absorption. The median time to peak plasma morphine levels (Tmax) was shorter for EMBEDA (7.5 hrs) compared to KADIAN® (10 hrs). Dose-related increase in steady-state pre-dose plasma concentrations of morphine were noted following multiple dose administration of EMBEDA in patients.

Food effect: While concurrent administration of high fat food decreases the rate and extent of morphine absorption from EMBEDA, the total bioavailability is not affected. Co-administration of a high-fat meal with EMBEDA did not compromise sequestration of naltrexone.

When taken as directed, the sequestered naltrexone in EMBEDA is not consistently absorbed into systemic circulation following single dose administration. In some subjects, a limited number (~2%) of blood samples had low and highly variable plasma naltrexone levels (median = 7.74 pg/mL, range 4.05-132 pg/mL) following single dose administration of 60 – 120 mg EMBEDA compared to oral naltrexone solution. In patients titrated up to 60 – 80 mg BID EMBEDA, naltrexone levels (4-25.5 pg/mL) were detected in 13 out of 67 patients at steady-state. In a long-term safety study where an average dose of EMBEDA was up to 860 mg administered twice a day for 12 months, 11.0% of blood samples at pre-dose timepoints at steady-state had detectable plasma naltrexone concentrations ranging from 4.03 to 145 pg/mL.

Compared to 2.4 mg naltrexone oral solution, which produced mean (SD) naltrexone plasma levels of 689 (+ 429 pg/mL) and mean (SD) 6β-naltrexol plasma levels of 3920 (+ 1350 pg/mL), administration of intact 60 mg EMBEDA produced no naltrexone plasma levels and mean (SD) 6β-naltrexol plasma levels of 16.7 (+ 13.5 pg/mL). Trough levels of plasma naltrexone and 6-β-naltrexol did not accumulate upon repeated administration of EMBEDA.

Tampering with the EMBEDA formulation by crushing or chewing the pellets, results in the rapid release and absorption of both morphine and naltrexone comparable to an oral solution. This has not been shown to reduce the abuse liability of EMBEDA.

Distribution

Once absorbed, morphine is distributed to skeletal muscle, kidneys, liver, intestinal tract, lungs, spleen, and brain. The volume of distribution of morphine is approximately 3 to 4 L/kg. Morphine is 30 to 35% reversibly bound to plasma proteins. Although the primary site of action of morphine is in the CNS, only small quantities pass the blood brain barrier. Morphine also crosses the placental membranes [see USE IN SPECIFIC POPULATIONS (8.1)] and has been found in breast milk [see USE IN SPECIFIC POPULATIONS (8.3)].

Metabolism

Major pathways of morphine metabolism include glucuronidation and sulfation in the liver to produce including morphine-3-glucuronide, M3G (about 50%) and morphine-6-glucuronide, M6G (about 5 to 15%) or morphine-3-etheral sulfate. A small fraction (less than 5%) of morphine is demethylated. M3G has no significant contribution to the analgesic activity. Although M6G does not readily cross the blood-brain barrier, it has been shown to have opioid agonist and analgesic activity in humans.

Naltrexone is extensively metabolized into 6-β-naltrexol.

Excretion

Approximately 10% of morphine dose is excreted unchanged in the urine. Elimination of morphine is primarily via hepatic metabolism to glucuronide metabolites M3G and M6G (55 to 65%) which are then renally excreted. A small amount of the glucuronide metabolites is excreted in the bile and there is some minor enterohepatic cycling.

The mean adult plasma clearance is about 20-30 mL/minute/kg. The effective half-life of morphine after IV administration is reported to be approximately 2.0 hours. The terminal elimination half-life of morphine following single dose EMBEDA administration is approximately 29 hours.

Special Populations

Geriatric: Pharmacokinetics of EMBEDA have not been investigated in elderly patients (greater than 65 years) although such patients were included in clinical studies. However, in a long-term open label safety study, the pre-dose plasma morphine concentrations after dose normalization were similar for subjects less than 65 years and those greater than or equal to 65 years of age [see USE IN SPECIFIC POPULATIONS (8.5)].

Pediatric: Pharmacokinetics of EMBEDA were not evaluated in pediatric population.

Gender: No meaningful differences were noted between male and female patients in the analysis of pharmacokinetic data of morphine from clinical studies.

Race: Pharmacokinetic differences due to race may exist. Additionally, Chinese subjects given intravenous morphine in one study had a higher clearance when compared to Caucasian subjects (1852 + 116 mL/min versus 1495 + 80 mL/min).

Hepatic Failure: The pharmacokinetics of morphine was found to be significantly altered in individuals with alcoholic cirrhosis. The clearance was found to decrease with a corresponding increase in half-life. The morphine-3-glucuronide (M3G) and morphine-6-glucuronide (M6G) to morphine plasma AUC ratios also decreased in these patients indicating a decrease in metabolic activity.

Renal Insufficiency: The pharmacokinetics of morphine is altered in renal failure patients. AUC is increased and clearance is decreased. The metabolites, M3G and M6G, accumulate several fold in renal failure patients compared with healthy subjects.

Drug Interaction/Alcohol Interaction: As such additive pharmacodynamic effects may be expected when EMBEDA is used in conjunction with alcohol, other opioids, or illicit drugs that cause central nervous system depression. Additionally, a pharmacokinetic drug interaction is noted with concomitant administration of 40% alcohol and EMBEDA, where an average 2-fold (range 1.4- to 5-fold increase) higher Cmax of morphine was noted compared to EMBEDA consumed with water

1 INDICATIONS AND USAGE

EMBEDA is an extended-release oral formulation of morphine sulfate and naltrexone hydrochloride indicated for the management of moderate to severe pain when a continuous, around-the-clock opioid analgesic is needed for an extended period of time.

EMBEDA is NOT intended for use as a prn analgesic.

EMBEDA is not indicated for acute/postoperative pain or if the pain is mild or not expected to persist for an extended period of time. EMBEDA is only indicated for postoperative use if the patient is already receiving chronic opioid therapy prior to surgery or if the postoperative pain is expected to be moderate to severe and persist for an extended period of time. Physicians should individualize treatment, moving from parenteral to oral analgesics as appropriate

4 CONTRAINDICATIONS

EMBEDA is contraindicated in patients with a known hypersensitivity to morphine, morphine salts, naltrexone, or in any situation where opioids are contraindicated.

4.1 Impaired Pulmonary Function

EMBEDA is contraindicated in patients with significant respiratory depression in unmonitored settings or the absence of resuscitative equipment.

EMBEDA is contraindicated in patients with acute or severe bronchial asthma or hypercapnia in unmonitored settings or the absence of resuscitative equipment [see WARNINGS AND PRECAUTIONS (5.1)].

4.2 Paralytic Ileus

EMBEDA is contraindicated in any patient who has or is suspected of having paralytic ileus.

5 WARNINGS AND PRECAUTIONS

EMBEDA is to be swallowed whole or the contents of the capsules sprinkled on apple sauce. The pellets in the capsules are not to be crushed, dissolved, or chewed. The resulting morphine dose may be fatal, particularly in opioid-naïve individuals. In opioid-tolerant individuals, the absorption of naltrexone may increase the risk of precipitating withdrawal.

EMBEDA 100 mg/4 mg is for use in opioid-tolerant patients only. Ingestion of these capsules or of the pellets within the capsules may cause fatal respiratory depression when administered to patients not already tolerant to high doses of opioids.

5.1 Misuse, Abuse, and Diversion of Opioids

EMBEDA contains morphine, an opioid agonist, and is a Schedule II controlled substance. Opioid agonists have the potential for being abused and are sought by drug abusers and people with addiction disorders and are subject to criminal diversion.

Morphine can be abused in a manner similar to other opioid agonists, legal or illicit. This should be considered when prescribing or dispensing EMBEDA in situations where the physician or pharmacist is concerned about an increased risk of misuse, abuse, or diversion.

Abuse of EMBEDA by crushing, chewing, snorting, or injecting the dissolved product will result in the uncontrolled delivery of the opioid and pose a significant risk to the abuser that could result in overdose and death [see DRUG ABUSE AND DEPENDENCE (9)].

Concerns about abuse and addiction should not prevent the proper management of pain. Healthcare professionals should contact their State Professional Licensing Board or State Controlled Substances Authority for information on how to prevent and detect abuse of this product.

5.2 Interactions with Alcohol and Drugs of Abuse

EMBEDA may be expected to have additive effects when used in conjunction with alcohol, other opioids, or illicit drugs that cause central nervous system depression because respiratory depression, hypotension, and profound sedation or coma may result.

Patients should not consume alcoholic beverages, prescription or non-prescription medications containing alcohol while on EMBEDA therapy. The co-ingestion of alcohol with EMBEDA can result in an increase of morphine plasma levels and potentially fatal overdose of morphine [see CLINICAL PHARMACOLOGY (12.3)].

5.3 Impaired Respiration

Respiratory depression is the chief hazard of all morphine preparations such as EMBEDA. Respiratory depression occurs more frequently and is more dangerous in elderly and debilitated patients, and those suffering from conditions accompanied by hypoxia, hypercapnia, or upper airway obstruction (when even moderate therapeutic doses may significantly decrease pulmonary ventilation).

EMBEDA should be used with extreme caution in patients with chronic obstructive pulmonary disease or cor pulmonale, and in patients having a substantially decreased respiratory reserve (e.g., severe kyphoscoliosis), hypoxia, hypercapnia, or pre-existing respiratory depression. In such patients, even usual therapeutic doses of morphine may increase airway resistance and decrease respiratory drive to the point of apnea. In these patients, alternative non-opioid analgesics should be considered, and opioids should be employed only under careful medical supervision at the lowest effective dose.

5.4 Head Injury and Increased Intracranial Pressure

The respiratory depressant effects of morphine with carbon dioxide retention and secondary elevation of cerebrospinal fluid pressure may be markedly exaggerated in the presence of head injury, other intracranial lesions, or a pre-existing increase in intracranial pressure. EMBEDA can produce effects on pupillary response and consciousness, which may obscure neurologic signs of further increases in pressure in patients with head injuries. EMBEDA should only be administered under such circumstances when considered essential and then with extreme care.

5.5 Hypotensive Effect

EMBEDA may cause severe hypotension. There is an added risk to individuals whose ability to maintain blood pressure has already been compromised by a reduced blood volume or a concurrent administration of drugs such as phenothiazines or general anesthetics [see DRUG INTERACTIONS (7.1)]. EMBEDA may produce orthostatic hypotension and syncope in ambulatory patients.

EMBEDA should be administered with caution to patients in circulatory shock, as vasodilation produced by the drug may further reduce cardiac output and blood pressure.

5.6 Interactions with other CNS Depressants

EMBEDA should be used with caution and in reduced dosage in patients who are concurrently receiving other central nervous system depressants including sedatives or hypnotics, general anesthetics, phenothiazines, other tranquilizers, and alcohol because respiratory depression, hypotension, and profound sedation or coma may result [see DRUG INTERACTIONS (7.1)].

5.7 Gastrointestinal Effects

EMBEDA should not be given to patients with gastrointestinal obstruction, particularly paralytic ileus, as there is a risk of the product remaining in the stomach for an extended period and the subsequent release of a bolus of morphine when normal gut motility is restored. As with other solid morphine formulations diarrhea may reduce morphine absorption.

The administration of morphine may obscure the diagnosis or clinical course in patients with acute abdominal condition.

5.8 Cordotomy

Patients taking EMBEDA who are scheduled for cordotomy or other interruption of pain transmission pathways should have EMBEDA ceased 24 hours prior to the procedure and the pain controlled by parenteral short-acting opioids. In addition, the post-procedure titration of analgesics for such patients should be individualized to avoid either oversedation or withdrawal syndromes.

5.9 Use in Pancreatic/Biliary Tract Disease

EMBEDA may cause spasm of the sphincter of Oddi and should be used with caution in patients with biliary tract disease, including acute pancreatitis. Opioids may cause increases in the serum amylase level.

5.10 Tolerance and Physical Dependence

Tolerance is the need for increasing doses of opioids to maintain a defined effect such as analgesia (in the absence of disease progression or other external factors). Physical dependence is manifested by withdrawal symptoms after abrupt discontinuation of a drug or upon administration of an antagonist. Physical dependence and tolerance are common during chronic opioid therapy.

The opioid abstinence or withdrawal syndrome is characterized by some or all of the following: restlessness, lacrimation, rhinorrhea, yawning, perspiration, chills, myalgia, and mydriasis. Other symptoms also may develop, including: irritability, anxiety, backache, joint pain, weakness, abdominal cramps, insomnia, nausea, anorexia, vomiting, diarrhea, or increased blood pressure, respiratory rate, or heart rate.

EMBEDA should not be abruptly discontinued [see DOSAGE AND ADMINISTRATION (2.5)].

5.11 Special Risk Groups

EMBEDA should be administered with caution, and in reduced dosages in elderly or debilitated patients; patients with severe renal or hepatic insufficiency; patients with Addison's disease; myxedema; hypothyroidism; prostatic hypertrophy or urethral stricture.

Caution should also be exercised in the administration of EMBEDA to patients with CNS depression, toxic psychosis, acute alcoholism, and delirium tremens.

All opioids may aggravate convulsions in patients with convulsive disorders, and all opioids may induce or aggravate seizures in some clinical settings.

5.12 Driving and Operating Machinery

EMBEDA may impair the mental and/or physical abilities needed to perform potentially hazardous activities such as driving a car or operating machinery. Patients must be cautioned accordingly. Patients should also be warned about the potential combined effects of EMBEDA with other CNS depressants, including other opioids, phenothiazines, sedative/hypnotics, and alcohol [see DRUG INTERACTIONS (7.1)].

5.13 Anaphylaxis

Although extremely rare, cases of anaphylaxis have been reported with the use of a similar extended release morphine formulation.

5.14 Accidentally Precipitated Withdrawal

Agonist/antagonist analgesics (i.e., pentazocine, nalbuphine, butorphanol) should be administered with caution to a patient who has received or is receiving a course of therapy with EMBEDA. In this situation, mixed agonist/antagonist analgesics may reduce the analgesic effect of EMBEDA and/or may precipitate withdrawal symptoms in these patients.

Consuming EMBEDA that have been tampered by crushing, chewing, or dissolving the extended-release formulation can release sufficient naltrexone to precipitate withdrawal in opioid-dependent individuals. Symptoms of withdrawal usually appear within five minutes of ingestion of naltrexone and can last for up to 48 hours. Mental status changes can include confusion, somnolence, and visual hallucinations. Significant fluid losses from vomiting and diarrhea can require intravenous fluid administration. Patients should be closely monitored and therapy with non-opioid medications tailored to meet individual requirements.

5.15 Laboratory Tests

Naltrexone does not interfere with thin-layer, gas-liquid, and high pressure liquid chromatographic methods which may be used for the separation and detection of morphine, methadone, or quinine in the urine. Naltrexone may or may not interfere with enzymatic methods for the detection of opioids depending on the specificity of the test. Please consult the test manufacturer for specific details.

6 ADVERSE REACTIONS

Serious adverse reactions that may be associated with EMBEDA therapy in clinical use include: respiratory depression, respiratory arrest, apnea, circulatory depression, cardiac arrest, hypotension, and/or shock [see OVERDOSAGE (10), WARNINGS AND PRECAUTIONS (5)].

The common adverse events seen on initiation of therapy with EMBEDA are dose dependent, and their frequency depends on the clinical setting, the patient's level of opioid tolerance, and host factors specific to the individual. They should be expected and managed as a part of opioid analgesia. The most frequent of these include drowsiness, dizziness, constipation, and nausea.

6.1 Clinical Studies Experience

Because clinical trials are conducted under widely varying conditions, adverse reaction rates observed in the clinical trials of a drug cannot be directly compared with rates in the clinical trials of another drug and may not reflect the rates observed in practice.

There were 1251 subjects exposed to at least one dose of EMBEDA in the clinical program. During late phase clinical development, 618 subjects received EMBEDA in two randomized, controlled, double-blind studies in subjects with osteoarthritis of the hip or knee. An additional 465 subjects received EMBEDA in an open-label, year-long safety study of subjects with chronic, non-cancer pain, 208 subjects for at least six months and 124 for 12 months. The remaining 168 subjects were exposed to a single dose of EMBEDA in early PK/PD studies.

Short-Term (12-Week) Randomized Study

Adverse reactions observed in at least 2% of subjects treated with EMBEDA

This study utilized an enriched enrollment with a randomized withdrawal design in which subjects were titrated to effect on open-label EMBEDA for up to 45 days. Once their pain was controlled, subjects were randomized to either active treatment with EMBEDA or were tapered off EMBEDA using a double-dummy design and placed on placebo. The Maintenance Period was 12 weeks. The most common adverse reactions leading to study discontinuation were nausea, constipation, vomiting, fatigue, dizziness, pruritus, and somnolence. Adverse reactions, defined as treatment-related adverse events assessed by the investigators, reported by greater than or equal to 2.0% of subjects in either the titration or maintenance phase of the 12-week study are presented in Table 1.

Long-Term Open-Label Safety Study

In the long-term open-label safety study, 465 patients with chronic non-malignant pain were enrolled and 124 patients were treated for up to 1 year. The distributions of adverse events were similar to that of the randomized, controlled studies, and were consistent with the most common opioid related adverse events. Adverse reactions, defined as treatment-related adverse events assessed by the investigators, reported by greater than or equal to 2.0% of subjects are presented in Table 2.

Adverse Reactions Observed in the Phase 2/3 Studies

Most common (greater than 10%): constipation, nausea, somnolence

Common (greater than or equal to 1% to less than 10%): vomiting, headache, dizziness, pruritus, dry mouth, diarrhea, fatigue, insomnia, hyperhidrosis, anxiety, chills, abdominal pain, lethargy, edema peripheral, dyspepsia, anorexia, muscle spasms, depression, flatulence, restlessness, decreased appetite, irritability, stomach discomfort, tremor, arthralgia, hot flush, sedation

Adverse Reactions Observed in the Phase 2/3 Studies

Most common (greater than or equal to 10%):

Gastrointestinal disorders: constipation, nausea;

Nervous system disorders: somnolence.

Common (greater than or equal to 1% to less than 10%):

Gastrointestinal disorders: abdominal pain, diarrhea, dry mouth, dyspepsia, flatulence, stomach discomfort, vomiting;

General disorders and administration site conditions: chills, edema peripheral, fatigue, irritability;

Metabolism and nutrition disorders: anorexia, decreased appetite;

Musculoskeletal and connective tissue disorders: arthralgia, muscle spasms;

Nervous system disorders: dizziness, headache, lethargy, sedation, tremor;

Psychiatric disorders: anxiety, depression, insomnia, restlessness;

Skin and subcutaneous tissue disorders: hyperhidrosis, pruritus;

Vascular disorders: hot flush.

Less Common (less than 1%):

Eye disorders: vision blurred, orthostatic hypotension;

Gastrointestinal disorders: abdominal distension, pancreatitis, abdominal discomfort, fecaloma, abdominal pain lower, abdominal tenderness;

General disorders and administration site conditions: malaise, asthenia, feeling jittery, drug withdrawal syndrome;

Hepatobiliary disorders: cholecystitis;

Investigations: alanine aminotransferase increased, aspartate aminotransferase increased;

Musculoskeletal and connective tissue disorders: myalgia, muscular weakness;

Nervous system disorders: depressed level of consciousness, mental impairment, memory impairment, disturbance in attention, stupor, paraesthesia, coordination abnormal;

Psychiatric disorders: disorientation, thinking abnormal, mental status changes, confusional state, euphoric mood, hallucination, abnormal dreams, mood swings, nervousness;

Renal and urinary disorders: urinary retention, dysuria;

Reproductive system and breast disorders: erectile dysfunction;

Respiratory, thoracic and mediastinal disorders: dyspnea, rhinorrhoea;

Skin and subcutaneous tissue disorders: rash, piloerection, cold sweat, night sweats;

Vascular disorders: hypotension, flushing.

10 OVERDOSAGE 10.1 Symptoms

Acute overdosage with morphine is manifested by respiratory depression, somnolence progressing to stupor or coma, skeletal muscle flaccidity, cold and clammy skin, constricted pupils, and, sometimes, pulmonary edema, bradycardia, hypotension, and death. Marked mydriasis rather than miosis may be seen due to severe hypoxia in overdose situations.

10.2 Treatment

Primary attention should be given to the re-establishment of a patent and protected airway and institution of assisted or controlled ventilation if needed. Other supportive measures (including oxygen, vasopressors) should be employed in the management of circulatory shock and pulmonary edema accompanying overdose as indicated. Cardiac arrest or arrhythmias will require advanced life support techniques.

The pure opioid antagonists, naloxone or nalmefene, are specific antidotes to respiratory depression which results from opioid overdose. Since the duration of reversal would be expected to be less than the duration of action of morphine in EMBEDA, the patient must be carefully monitored until spontaneous respiration is reliably re-established. EMBEDA will continue to release and add to the morphine load for up to 24 hours after administration and the management of an overdose should be monitored accordingly. If the response to opioid antagonists is suboptimal or not sustained, additional antagonist should be given as directed by the manufacturer of the product.

Opioid antagonists should not be administered in the absence of clinically significant respiratory or circulatory depression secondary to morphine overdose. Such agents should be administered cautiously to persons who are known, or suspected to be physically dependent on EMBEDA. In such cases, an abrupt or complete reversal of opioid effects may precipitate an acute withdrawal syndrome.

The sequestered naltrexone in EMBEDA has no role in the treatment of opioid overdose.

In an individual physically dependent on opioids, administration of an opioid receptor antagonist may precipitate an acute withdrawal. The severity of the withdrawal produced will depend on the degree of physical dependence and the dose of the antagonist administered. Use of an opioid antagonist should be reserved for cases where such treatment is clearly needed. If it is necessary to treat serious respiratory depression in the physically dependent patient, administration of the antagonist should be begun with care and by titration with smaller than usual doses of the antagonist

2 DOSAGE AND ADMINISTRATION

Selection of patients for treatment with morphine sulfate should be governed by the same principles that apply to the use of similar opioid analgesics. Physicians should individualize treatment in every case, using non-opioid analgesics, opioids on an as needed basis and/or combination products, and chronic opioid therapy in a progressive plan of pain management such as outlined by the World Health Organization and Federation of State Medical Boards Model Guidelines.

Care should be taken to use low initial doses of EMBEDA in patients who are not already opioid-tolerant, especially those who are receiving concurrent treatment with muscle relaxants, sedatives, or other CNS active medications.

The 100 mg/4 mg capsules are for use only in opioid-tolerant patients.

EMBEDA is to be swallowed whole or the contents of the capsules sprinkled on apple sauce and taken by mouth. The pellets in the capsules are not to be crushed, dissolved, or chewed before swallowing.

2.1 Initiating Therapy with EMBEDA

It is critical to adjust the dosing regimen for each patient individually, taking into account the patient's prior analgesic treatment experience. In the selection of the initial dose of EMBEDA, attention should be given to:

1) the total daily dose, potency, and kind of opioid the patient has been taking previously;
2) the reliability of the relative potency estimate used to calculate the equivalent dose of morphine needed (Note: potency estimates may vary with the route of administration);
3) the patient's degree of opioid experience and opioid tolerance;
4) the general condition and medical status of the patient;
5) concurrent medication;
6) the type and severity of the patient's pain.

The following dosing recommendations can be considered approaches to what is actually a series of clinical decisions over time in the management of the pain of an individual patient:

Use of EMBEDA as the First Opioid Analgesic

The lowest dose of EMBEDA should be used as the initial opioid analgesic in patients with chronic pain. Patients may subsequently be titrated to a once or twice a day dosage which adequately manages their pain.

Conversion from Other Oral Morphine Formulations to EMBEDA

Patients on other oral morphine formulations may be converted to EMBEDA by administering one-half of the patient's total daily oral morphine dose as EMBEDA every 12 hours (twice-a-day) or by administering the total daily oral morphine dose as EMBEDA every 24 hours (once-a-day). EMBEDA should not be given more frequently than every 12 hours.

Conversion from Oral Opioids, Parenteral Morphine, or Other Parenteral Opioids to EMBEDA

EMBEDA can be administered to patients previously receiving treatment with parenteral morphine or other opioids. While there are useful tables of oral and parenteral equivalents in cancer analgesia, there is substantial inter-patient variation in the relative potency of different opioid drugs and formulations. For these reasons, it is better to underestimate the patient's 24-hour oral morphine requirement and provide rescue medication than to overestimate and manage an adverse event. The following general points should be considered:

1. Parenteral to Oral Morphine Ratio: It may take anywhere from 2-6 mg of oral morphine to provide analgesia equivalent to 1 mg of parenteral morphine. A dose of oral morphine three times the daily parenteral morphine requirement may be sufficient in chronic use settings.
2. Other Oral or Parenteral Opioids to Oral Morphine Sulfate: There is lack of systematic evidence bearing on these types of analgesic substitutions. Therefore, specific recommendations are not possible. Physicians are advised to refer to published relative potency data, keeping in mind that such ratios are only approximate. In general, it is safest to give half of the estimated daily morphine demand as the initial dose and to manage inadequate analgesia by supplementation with immediate-release morphine.

The first dose of EMBEDA may be taken with the last dose of any immediate-release (short-acting) opioid medication due to the extended-release characteristics of EMBEDA.

2.2 Individualization of Dosage

Patients may develop some degree of tolerance, requiring dosage adjustment until they have achieved their individual balance between effective analgesia and opioid side effects such as confusion, sedation, and constipation.

- EMBEDA should be titrated no more frequently than every-other-day to allow patients to stabilize before escalating the dose.
- If breakthrough pain occurs, the dose may be supplemented with a small dose (less than 20% of the total daily dose) of a short-acting analgesic.
- Patients who exhibit signs of excessive opioid side effects such as sedation should have their dose reduced.
- Patients who experience inadequate analgesia on once-daily dosing should be switched to twice-a-day.
- EMBEDA should not be dosed more frequently than every 12 hours.

During periods of changing analgesic requirements including initial titration, frequent communication is recommended between physician, other members of the healthcare team, the patient, and the caregiver/family.

2.3 Alternative Methods of Administration

Patients who have difficulty swallowing whole capsules or tablets may benefit from an alternative method of administration. EMBEDA pellets may be sprinkled over apple sauce. Other foods have not been tested and should not be substituted for apple sauce.

1. Sprinkle the pellets onto a small amount of apple sauce and use immediately.
2. The patient must be cautioned not to chew the pellets [see WARNINGS AND PRECAUTIONS (5)].
3. Rinse mouth to ensure all pellets have been swallowed.
4. Patients should consume entire portion and should not divide apple sauce into separate doses.

Do not administer EMBEDA pellets through a nasogastric or gastric tubes.

2.4 Maintenance of Therapy

Continual re-evaluation of the patient receiving morphine sulfate is important, with special attention to the maintenance of pain control and the relative incidence of side effects associated with therapy. If the level of pain increases, effort should be made to identify the source of increased pain, while adjusting the dose as described above to decrease the level of pain. During chronic therapy, especially for non-cancer-related pain (or pain associated with other terminal illnesses), the continued need for the use of opioid analgesics should be re-assessed as appropriate.

2.5 Cessation of Therapy

In general, EMBEDA should not be abruptly discontinued. However, EMBEDA, like other opioids, can be safely discontinued without the development of withdrawal symptoms by slowly tapering the daily dose.

HOW SUPPLIED/STORAGE AND HANDLING

 | EMBEDA 20 mg/0.8 mg | EMBEDA 30 mg/1.2 mg | EMBEDA 50 mg/2 mg | EMBEDA 60 mg/2.4 mg | EMBEDA 80 mg/3.2 mg | EMBEDA 100 mg/4 mg
Morphine sulfate | 20 mg | 30 mg | 50 mg | 60 mg | 80 mg | 100 mg
Sequestered naltrexone hydrochloride | 0.8 mg | 1.2 mg | 2 mg | 2.4 mg | 3.2 mg | 4 mg
Capsule Description | size 4, two-toned, yellow opaque hard gelatin capsule. The darker-toned cap has “EMBEDA” printed in grey ink and a single grey band around ¾ of the circumference. The lighter-toned body has “20” reverse-printed in a grey circle. | size 3, two-toned, blue violet opaque hard gelatin capsule. The darker-toned cap has “EMBEDA” printed in grey ink and a single grey band around ¾ of the circumference. The lighter-toned body has “30” reverse-printed in a grey circle. | size 1, two-toned, blue opaque hard gelatin capsule. The darker-toned cap has “EMBEDA” printed in grey ink and a single grey band around ¾ of the circumference. The lighter-toned body has “50” reverse-printed in a grey circle. | size 0, two-toned, pink opaque hard gelatin capsule. The darker-toned cap has “EMBEDA” printed in grey ink and a single grey band around ¾ of the circumference. The lighter-toned body has “60” reverse-printed in a grey circle. | size 0, two-toned, light peach opaque elongated hard gelatin capsule. The darker-toned cap has “EMBEDA” printed in grey ink and a single grey band around ¾ of the circumference. The lighter-toned body has “80” reverse-printed in a grey circle. | size 00, two-toned, green opaque hard gelatin capsule. The darker-toned cap has “EMBEDA” printed in grey ink and a single grey band around ¾ of the circumference. The lighter-toned body has “100” reverse-printed in a grey circle.
Bottle Size | 100 | 100 | 100 | 100 | 100 | 100
NDC # | 60793-430-01 | 60793-431-01 | 60793-433-01 | 60793-434-01 | 60793-435-01 | 60793-437-01

Store at 25°C (77°F); excursions permitted between 15° and 30°C (59° and 86°F).

Dispense in a sealed, tamper-evident, childproof, light-resistant container.

17 PATIENT COUNSELING INFORMATION

Patients receiving EMBEDA should be given the following instructions by the physician:

- Patients should be advised that EMBEDA contains morphine and naltrexone and should be taken only as directed.

- The dose of morphine sulfate should not be adjusted without consulting with a physician or other healthcare professional. EMBEDA should be swallowed whole (not crushed, dissolved, or chewed) due to a risk of fatal morphine overdose or naltrexone precipitated withdrawal symptoms. Alternately, EMBEDA Capsules may be opened and the entire contents sprinkled on a small amount of apple sauce immediately prior to ingestion [see DOSAGE AND ADMINISTRATION (2.3)].

- Patients should not consume alcoholic beverages while on EMBEDA therapy. Additionally, patients must not use prescription or non-prescription medications containing alcohol while on EMBEDA therapy. The co-ingestion of alcohol with EMBEDA may result in an increase of plasma levels and potentially fatal overdose of morphine.

- Patients should be advised of the most common adverse reactions that may occur while taking EMBEDA: constipation, nausea, somnolence, vomiting, dizziness, pruritus, and headache.

- Patients should be advised that EMBEDA may cause drowsiness, dizziness, or lightheadedness and may impair mental and/or physical ability required for the performance of potentially hazardous tasks (e.g., driving, operating machinery). Patients started on EMBEDA or patients whose dose has been adjusted should refrain from any potentially dangerous activity until it is established that they are not adversely affected.

- Patients should not combine EMBEDA with central nervous system depressants (sleep aids, tranquilizers) except by the orders of the prescribing physician because dangerous additive effects may occur resulting in serious injury or death.

- Patients should be advised that EMBEDA is a potential drug of abuse. They should protect it from theft.

- Special care must be taken to avoid accidental ingestion or use by individuals (including children) other than the patient for whom it was originally prescribed, as such unsupervised use may have severe, even fatal, consequences [see WARNINGS AND PRECAUTIONS (5)].
- Patients should be advised that EMBEDA 100 mg/4 mg is for use only in opioid-tolerant patients.

- Women of childbearing potential who become or are planning to become pregnant should consult a physician prior to initiating or continuing therapy with EMBEDA.

- Safe use in pregnancy has not been established. Prolonged use of opioid analgesics during pregnancy may cause fetal neonatal physical dependence, and neonatal withdrawal may occur.

- As with other opioids, patients taking EMBEDA should be advised of the potential for severe constipation; appropriate laxatives and/or stool softeners as well as other appropriate treatments should be initiated from the onset of opioid therapy.

- Patients should be advised to seek medical attention immediately if signs of a serious allergic reaction occur, such as swelling of the face, throat, or tongue, trouble breathing, feeling dizzy or faint, pounding heart beat, chest pain or feeling of doom [see WARNINGS AND PRECAUTIONS (5.13)].

17.1 Breakthrough Pain/Adverse Experiences

Patients should be advised to report episodes of breakthrough pain and adverse experiences occurring during therapy. Individualization of dosage is essential to make optimal use of this medication.

17.2 Mental and/or Physical Ability

Patients should be advised that EMBEDA may impair mental and/or physical ability required for the performance of potentially hazardous tasks (e.g., driving, operating machinery). Patients started on EMBEDA or whose dose has been changed should refrain from dangerous activity until it is established that they are not adversely affected [see WARNINGS AND PRECAUTIONS (5.12)].

17.3 Avoidance of Alcohol or Other CNS Depressants

Patients should be advised that EMBEDA should not be taken with alcohol, prescription or non-prescription medications containing alcohol, or other CNS depressants (sleeping medication, tranquilizers) except by the orders of the prescribing healthcare provider because dangerous additive effects may occur resulting in serious injury or death [see WARNINGS AND PRECAUTIONS (5.2),(5.6)].

17.4 Pregnancy

Women of childbearing potential who become or are planning to become pregnant, should consult their prescribing healthcare provider prior to initiating or continuing therapy with EMBEDA [see USE IN SPECIFIC POPULATIONS (8.1)].

17.5 Cessation of Therapy

Patients should be advised that if they have been receiving treatment with EMBEDA for more than a few weeks and cessation of therapy is indicated, it may be appropriate to taper the EMBEDA dose, rather than abruptly discontinue it, due to the risk of precipitating withdrawal symptoms. Their prescribing healthcare provider should provide a dose schedule to accomplish a gradual discontinuation of the medication.

17.6 Drug of Abuse

Patients should be advised that EMBEDA is a potential drug of abuse. They should protect it from theft, and it should never be given to anyone other than the individual for whom it was prescribed [see WARNINGS AND PRECAUTIONS (5.1)].

17.7 Constipation

Patients should be advised that severe constipation could occur as a result of taking EMBEDA and appropriate laxatives, stool softeners and other appropriate treatments should be initiated from the beginning of opioid therapy.

17.8 Storage/Destruction of Unused EMBEDA

Patients should be instructed to keep EMBEDA in a secure place out of the reach of children. When EMBEDA is no longer needed, the unused capsules should be destroyed by flushing down the toilet.

17.9 FDA-Approved Patient Labeling

[See separate leaflet.]

Manufactured for: King Pharmaceuticals, Inc., 501 Fifth Street, Bristol, TN 37620

(Telephone: 1-800-776-3637)

by: Actavis Elizabeth LLC, 200 Elmora Avenue, Elizabeth, NJ 07207 USA

EMBEDA is a trademark of Alpharma Pharmaceuticals LLC, a wholly owned subsidiary of King Pharmaceuticals, Inc.

KADIAN is a registered trademark of Actavis Elizabeth LLC

To report SUSPECTED ADVERSE REACTIONS, contact King Pharmaceuticals, Inc. at 1-800-546-4905 or DSP@Kingpharm.com or FDA at 1-800-FDA-1088 or www.fda.gov/medwatch

U.S. Patent Numbers:

5,202,128

5,378,474

5,330,766

40-9096

Revised – June 2009

v.10

WARNING

EMBEDA™ capsules contain morphine, an opioid agonist and a Schedule II controlled substance with an abuse liability similar to other opioid agonists. EMBEDA can be abused in a manner similar to other opioid agonists, legal or illicit. This should be considered when prescribing or dispensing EMBEDA in situations where the physician or pharmacist is concerned about an increased risk of misuse, abuse, or diversion.

EMBEDA contains pellets of an extended-release oral formulation of morphine sulfate, an opioid receptor agonist, surrounding an inner core of naltrexone hydrochloride, an opioid receptor antagonist indicated for the management of moderate to severe pain when a continuous, around-the-clock opioid analgesic is needed for an extended period of time.

EMBEDA is NOT intended for use as a prn analgesic.

EMBEDA 100 mg/4 mg IS FOR USE IN OPIOID-TOLERANT PATIENTS ONLY. Ingestion of these capsules or the pellets within the capsules may cause fatal respiratory depression when administered to patients not already tolerant to high doses of opioids.

Patients should not consume alcoholic beverages while on EMBEDA therapy. Additionally, patients must not use prescription or non-prescription medications containing alcohol while on EMBEDA therapy. The co-ingestion of alcohol with EMBEDA may result in an increase of plasma levels and potentially fatal overdose of morphine. EMBEDA is to be swallowed whole or the contents of the capsules sprinkled on apple sauce. The pellets in the capsules are not to be crushed, dissolved, or chewed due to the risk of rapid release and absorption of a potentially fatal dose of morphine.

Crushing, chewing, or dissolving EMBEDA will also result in the release of naltrexone which may precipitate withdrawal in opioid-tolerant individuals.

17.9 FDA-Approved Patient Labeling

[See separate leaflet.]

Manufactured for: King Pharmaceuticals, Inc., 501 Fifth Street, Bristol, TN 37620

(Telephone: 1-800-776-3637)

by: Actavis Elizabeth LLC, 200 Elmora Avenue, Elizabeth, NJ 07207 USA

EMBEDA is a trademark of Alpharma Pharmaceuticals LLC, a wholly owned subsidiary of King Pharmaceuticals, Inc.

KADIAN is a registered trademark of Actavis Elizabeth LLC

To report SUSPECTED ADVERSE REACTIONS, contact King Pharmaceuticals, Inc. at 1-800-546-4905 or DSP@Kingpharm.com or FDA at 1-800-FDA-1088 or www.fda.gov/medwatch

U.S. Patent Numbers:

5,202,128

5,378,474

5,330,766

40-9096

Revised – June 2009

MEDICATION GUIDE

EMBEDA™ (im-bed-a)
(morphine sulfate and naltrexone hydrochloride)
Extended Release Capsules CII

IMPORTANT: Keep EMBEDA in a safe place away from children. Accidental use by a child is a medical emergency and can result in death. If a child accidentally takes EMBEDA, get emergency help right away.

Read the Medication Guide that comes with EMBEDA before you start taking it and each time you get a new prescription. There may be new information. This information does not take the place of talking with your healthcare provider about your medical condition or your treatment. Share this important information with members of your household.

What Is the Most Important Information I Should Know About EMBEDA?

- Do not crush, dissolve, or chew EMBEDA capsules or the capsule contents before swallowing. If EMBEDA is taken in this way, both the morphine and naltrexone in EMBEDA will be released too fast. This is dangerous. It may cause you to have trouble breathing, and lead to death.
  - If your body is not used to taking opioids and your body absorbs too much morphine, you could overdose and die.
  - If you have been taking opioids (narcotics) for a period of time, and your body absorbs the naltrexone in EMBEDA, this could cause you to have uncomfortable withdrawal symptoms.
- Take EMBEDA exactly as prescribed by your healthcare provider.
- EMBEDA is not for use to treat pain that you only have once in a while (“as needed”).
- If you cannot swallow capsules, tell your healthcare provider. There may be another way to take EMBEDA that may be right for you. See “How should I take EMBEDA?”
- Do not take the highest dose of EMBEDA (morphine sulfate 100 mg and naltrexone hydrochloride 4 mg) unless you are “opioid tolerant.” Opioid tolerant means that you regularly use another opioid medicine for your constant (around the clock) pain and your body is used to it.
- Do not drink alcohol, or use prescription or non-prescription medicines that contain alcohol while you are being treated with EMBEDA. Alcohol can cause very high levels of morphine in your blood and you can die due to an overdose of morphine.
- Prevent theft, misuse or abuse. Keep EMBEDA in a safe place to protect it from being stolen. EMBEDA can be a target for people who misuse or abuse prescription medicines or street drugs.
- Never give EMBEDA to anyone else, even if they have the same symptoms you have. It may harm them or even cause death.

See the section “What are the possible side effects of EMBEDA?” for more information about side effects.

What is EMBEDA?

- EMBEDA is a prescription medicine that contains morphine sulfate, an opioid receptor agonist (narcotic pain medicine) and naltrexone hydrochloride, an opioid receptor antagonist. Naltrexone hydrochloride is in the middle of each pellet and has a special coating to protect it from being released. If you crush or chew EMBEDA, the naltrexone will be released all at one time. See “What is the most important information I should know about EMBEDA?
- EMBEDA is a federally controlled substance (CII) because it is a strong opioid pain medicine that can be abused by people who abuse prescription medicines or street drugs.
- EMBEDA is used to manage moderate to severe pain that continues around-the-clock and is expected to last for a long period of time.
- It is not known if EMBEDA is safe and works in children under the age of 18.

Who Should Not Take EMBEDA?

Do not take EMBEDA if you:

- are having an asthma attack or have severe asthma, trouble breathing, or lung problems.
- have a bowel blockage called paralytic ileus.
- are allergic to morphine, morphine salts, naltrexone, or any of the ingredients in EMBEDA. See the end of this Medication Guide for a complete list of ingredients in EMBEDA.

What Should I Tell My Healthcare Provider Before Starting EMBEDA?

- EMBEDA may not be right for you. Tell your healthcare provider about all of your medical conditions, especially if you:
  - have trouble breathing or lung problems
  - have a head injury or brain problem
  - have liver or kidney problems
  - have adrenal gland problems, such as Addison’s disease
  - have convulsions or seizures
  - have thyroid problems
  - have problems urinating or prostate problems
  - have constipation or other bowel problems
  - have problems with your pancreas or gallbladder
  - have severe scoliosis
  - have a drinking problem or alcoholism
  - have severe mental problems or hallucinations (see or hear things that are not really there)
  - have or have had drug abuse or drug addiction problems
  - are planning to have surgery (cordotomy) or another procedure that will interrupt the pain signals to your body.
  - are pregnant or plan to become pregnant. EMBEDA may harm your unborn baby.
  - are breastfeeding. EMBEDA may pass through your milk and may harm your baby. You should not breastfeed while taking EMBEDA.
  - Tell your healthcare provider about all the medicines you take, including prescription and nonprescription medicines, vitamins, and herbal supplements. Some medicines may cause serious problems when taken with EMBEDA. Sometimes, the doses of certain medicines and EMBEDA may need to be changed if used together.
  - Be especially careful about taking other medicines that make you sleepy such as:
    - other pain medicines
    - anti-depressant medicines
    - sleeping pills
    - anti-anxiety medicines
    - muscle relaxants
    - antihistamines
    - anti-nausea medicines
    - tranquilizers
    Also tell your healthcare provider if you take:
    - cimetidine (Tagamet)
    - a water pill (diuretic)
    - an anticholinergic medicine
  - Do not take EMBEDA if you already take a monoamine oxidase inhibitor medicine (MAOI) or within 14 days after you stop taking an MAOI medicine.
  - Do not take any new medicine while using EMBEDA until you have talked to your healthcare provider or pharmacist. They will tell you if it is safe to take other medicines with EMBEDA.

Ask your healthcare provider if you are not sure if your medicine is one listed above.

Know the medicines you take. Keep a list of them to show your healthcare provider and pharmacist when you get a new medicine.

How Should I Take EMBEDA?

- Take EMBEDA exactly as prescribed by your healthcare provider. Do not change your dose unless your healthcare provider tells you to.
- You can take EMBEDA with or without food.
- Swallow EMBEDA capsule whole. Do not crush, dissolve, or chew EMBEDA or the pellets in the capsules before swallowing. See “What is the most important information I should know about EMBEDA?”
- If you cannot swallow capsules, tell your healthcare provider. There may be another way to take EMBEDA that may be right for you. If your doctor tells you that you can take EMBEDA using this other way, follow these steps:

EMBEDA can be opened and the pellets inside the capsule can be sprinkled over apple sauce, as follows:

- Open the EMBEDA capsule and sprinkle the pellets over approximately one tablespoon of apple sauce (Figure 1).
  Figure 1 Swallow all of the apple sauce and pellets right away. Do not save any of the apple sauce and pellets for another dose (Figure 2).
  Figure 2 Rinse your mouth to make sure you have swallowed all of the pellets. Do not chew the pellets (Figure 3).
  Figure 3 Flush the empty capsule down the toilet right away (Figure 4).
  Figure 4 You should not receive EMBEDA through a nasogastric tube or gastric tube (stomach tube).
- If you miss a dose, take it as soon as possible. If it is almost time for your next dose, skip the missed dose. Just take the next dose at your regular time. Do not take 2 doses at the same time unless your healthcare provider tells you to. If you are not sure about your dosing, call your healthcare provider.
- If you take too much EMBEDA or overdose, call 911 or poison control center right away.
- Call your healthcare provider if the dose of EMBEDA that you are taking does not relieve your pain.

What Should I Avoid While Taking EMBEDA?

- Do not drive, operate heavy machinery, or do other dangerous activities, especially when you start taking EMBEDA and when your dose is changed, until you know how you react to this medicine. EMBEDA can make you sleepy, and also cause you to feel dizzy and lightheaded. Ask your healthcare provider to tell you when it is okay to do these activities.

What are the Possible Side Effects of EMBEDA?

EMBEDA can cause serious side effects, including:

- See “What is the most important information I should know about EMBEDA?”
- EMBEDA can cause serious breathing problems that can become life-threatening, especially if used the wrong way.
  Call your healthcare provider or get medical help right away if:
  - your breathing slows down
  - you have shallow breathing (little chest movement with breathing)
  - you feel faint, dizzy, confused, or
  - have any other unusual symptoms

These can be symptoms that you have taken too much EMBEDA (overdose) or the dose is too high for you. These symptoms may lead to serious problems or death if not treated right away.

- EMBEDA can cause your blood pressure to drop. This can make you feel dizzy and faint if you get up too fast from sitting or lying down. Low blood pressure is also more likely to happen if you take other medicines that can also lower your blood pressure. Severe low blood pressure can happen if you lose blood or take certain other medicines.

- EMBEDA can cause physical dependence. Do not stop taking EMBEDA or any other opioid without talking to your healthcare provider. You could become sick with uncomfortable withdrawal symptoms because your body has become used to these medicines. Physical dependence is not the same as drug addiction.

- There is a chance of abuse or addiction with EMBEDA. The chance is higher if you are or have been addicted to or abused other medicines, street drugs, or alcohol, or if you have a history of mental problems.

- Serious allergic reactions. Rarely, severe allergic reactions happen in people who take a long-acting morphine medicine that is like EMBEDA. Get medical help right away if you have any of these symptoms of a severe allergic reaction:
  - feel dizzy or faint
  - trouble breathing
  - pounding heart beat
  - chest pain
  - swelling of the face, throat, or tongue
  - feeling of doom
  The most common side effects of EMBEDA are
  - constipation
  - nausea
  - sleepiness
  - vomiting
  - dizziness
  - itching
  - headache
    These side effects may decrease with continued use. Talk to your healthcare provider if you continue to have these side effects. These are not all the possible side effects of EMBEDA. For a complete list, ask your healthcare provider or pharmacist.
    Constipation (not often enough or hard bowel movements) is a common side effect of pain medicines (opioids) including EMBEDA and is unlikely to go away without treatment. Talk to your healthcare provider about dietary changes, and the use of laxatives (medicines to treat constipation) and stool softeners to prevent or treat constipation while taking EMBEDA.
    Talk to your healthcare provider if you have any side effects that bother you or do not go away.
    These are not all the possible side effects of EMBEDA. For more information, ask your healthcare provider or pharmacist.
    Call your doctor for medical advice about side effects. You may report side effects to FDA at 1-800-FDA-1088.
  - Selling or giving away this medicine is against the law
  How should I store EMBEDA?
  - See “What is the most important information I should know about EMBEDA?"
  - Keep EMBEDA out of the reach of children.
  - Keep EMBEDA in the container it comes in.
  - Keep EMBEDA at room temperature between 59° to 86°F (15° to 30°C).
  - After you stop taking EMBEDA, flush the unused capsules down the toilet.

General Information about EMBEDA

Medicines are sometimes prescribed for purposes other than those listed in a Medication Guide. Do not use EMBEDA for conditions for which it was not prescribed. Do not give EMBEDA to other people, even if they have the same symptoms you have. It may harm them and even cause death. Sharing EMBEDA is against the law.

This medication guide summarizes the most important information about EMBEDA. If you would like more information, talk with your healthcare provider. Also, you can ask your pharmacist or healthcare provider for information about EMBEDA that is written for healthcare professionals. For more information call 1-800-776-3637 or go to www.kingpharm.com.

What are the ingredients in EMBEDA?

Active Ingredients: pellets of morphine sulfate and naltrexone hydrochloride

Inactive Ingredients common to all strengths: talc, ammonio methacrylate copolymer, sugar spheres, ethylcellulose, sodium chloride, polyethylene glycol, hydroxypropyl cellulose, dibutyl sebacate, methacrylic acid copolymer, diethyl phthalate, magnesium stearate, sodium lauryl sulfate, and ascorbic acid. The capsule shells contain gelatin, titanium dioxide, and grey ink, D and C yellow #10 (EMBEDA 20 mg/0.8 mg), FD and C red #3, FD and C blue #1 (EMBEDA 30 mg/1.2 mg), D and C red #28, FD and C red #40, FD and C blue #1 (EMBEDA 50 mg/2 mg), D and C red #28, FD and C red #40, FD and C blue #1 (EMBEDA 60 mg/2.4 mg), FD and C blue #1, FD and C red #40, FD and C yellow #6 (EMBEDA 80 mg/3.2 mg), D and C yellow #10, FD and C blue #1 (EMBEDA 100 mg/4 mg).

Manufactured for: King Pharmaceuticals, Inc., 501 Fifth Street, Bristol, TN 37620

(Telephone: 1-800-776-3637)

by: Actavis Elizabeth LLC, 200 Elmora Avenue, Elizabeth, NJ 07207 USA

EMBEDA is a trademark of Alpharma Pharmaceuticals LLC, a wholly owned subsidiary of King Pharmaceuticals, Inc.

41-1126

Revision: June 2009

This Medication Guide has been approved by the U.S. Food and Drug Administration

v.10